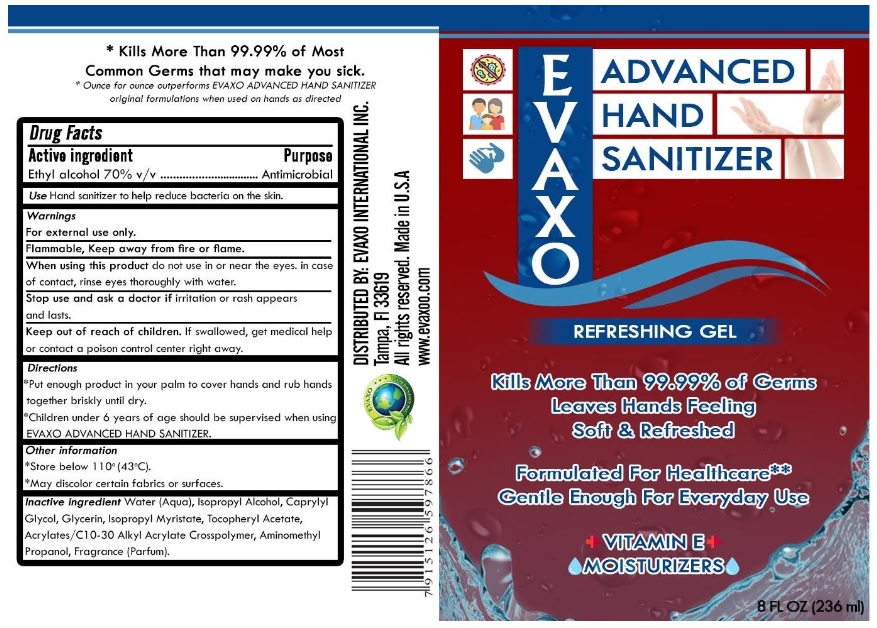 DRUG LABEL: EVAXO ADVANCED HAND SANITIZER
NDC: 78376-237 | Form: GEL
Manufacturer: Evaxo International Inc
Category: otc | Type: HUMAN OTC DRUG LABEL
Date: 20200602

ACTIVE INGREDIENTS: ALCOHOL 70 mL/100 mL
INACTIVE INGREDIENTS: WATER; ISOPROPYL ALCOHOL; CAPRYLYL GLYCOL; GLYCERIN; ISOPROPYL MYRISTATE; .ALPHA.-TOCOPHEROL ACETATE; CARBOMER INTERPOLYMER TYPE A (ALLYL SUCROSE CROSSLINKED); AMINOMETHYLPROPANOL

EVAXO ADVANCED HAND SANITIZER

Active ingredient

Ethyl alcohol 70% v/v

Purpose

Antimicrobial

INDICATIONS AND USAGE

Use Hand sanitizer to help reduce bacteria on the skin.

Warnings

For external use only.

Flammable, Keep away from fire or flame.

When using this product do not use in or near the eyes. in case of contact, rinse eyes thoroughly with water.

Stop use and ask a doctor if irritation or rash appears and lasts.

Keep out of reach of children. If swallowed, get medical help or contact poison control center right away.

Directions

*Put enough product in your palm to cover hands and rub hands together briskly until dry.

*Children under 6 years of age should be supervised when using EVAXO ADVANCED HAND SANITIZER.

Other information

*Store below 110° (43°C).

*May discolor certain fabrics or surfaces.

Inactive ingredient Water (Aqua), Isopropyl Alcohol, Caprylyl Glycol, Glycerin, Isopropyl Myristate, Tocopheryl Acetate, Acrylates/ C10-30 Alkyl Acrylate Crosspolymer, Aminomethyl Propanol, Fragrance (Parfum).

ALOE

REFRESHING GEL

Kills More Than 99.99% of Germs

Leaves Hands Feeling Soft & Refreshed

Formulated For Healthcare**

Gentle Enough For Everyday Use

VITAMIN E

MOISTURIZERS

* Kills More Than 99.99% of Most Common Germs that may make you sick.

* Ounce for ounce outperforms EVAXO ADVANCED HAND SANITIZER original formulations when used on hands as directed

THE GREEN SOURCES

DISTRIBUTED BY: EVAXO INTERNATIONAL INC.

Tampa, FI 33619

All rights reserved. Made in U.S.A